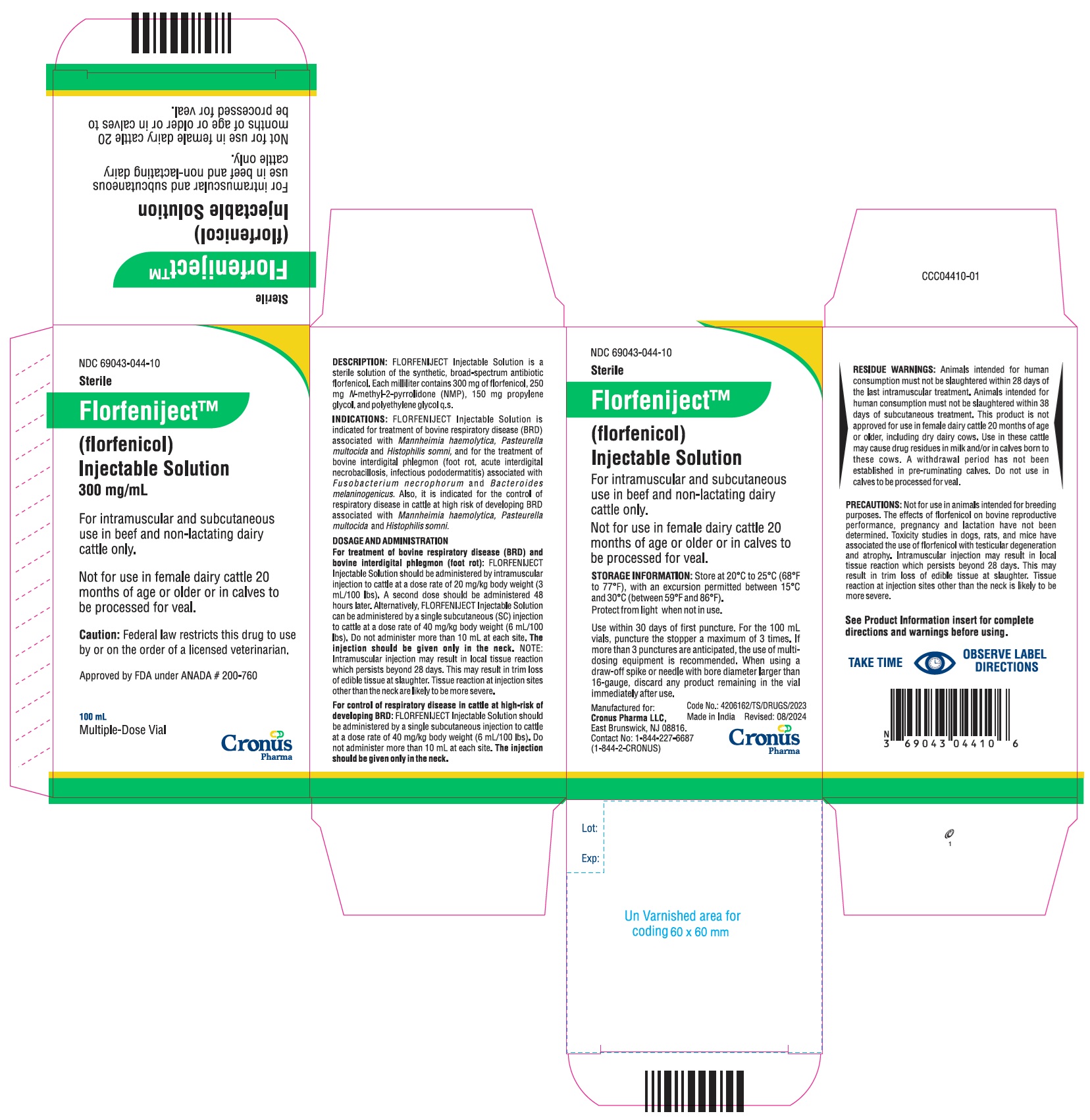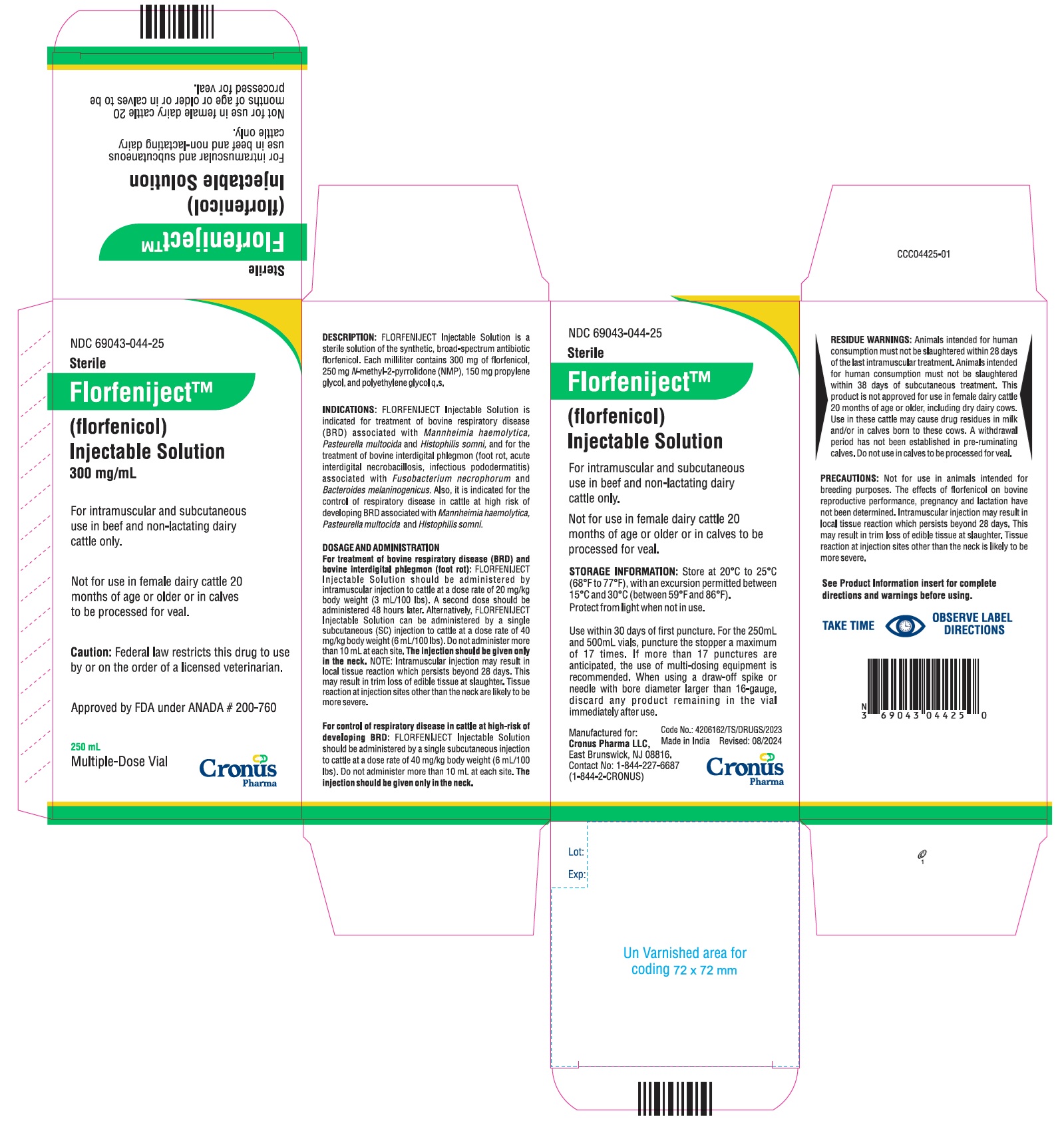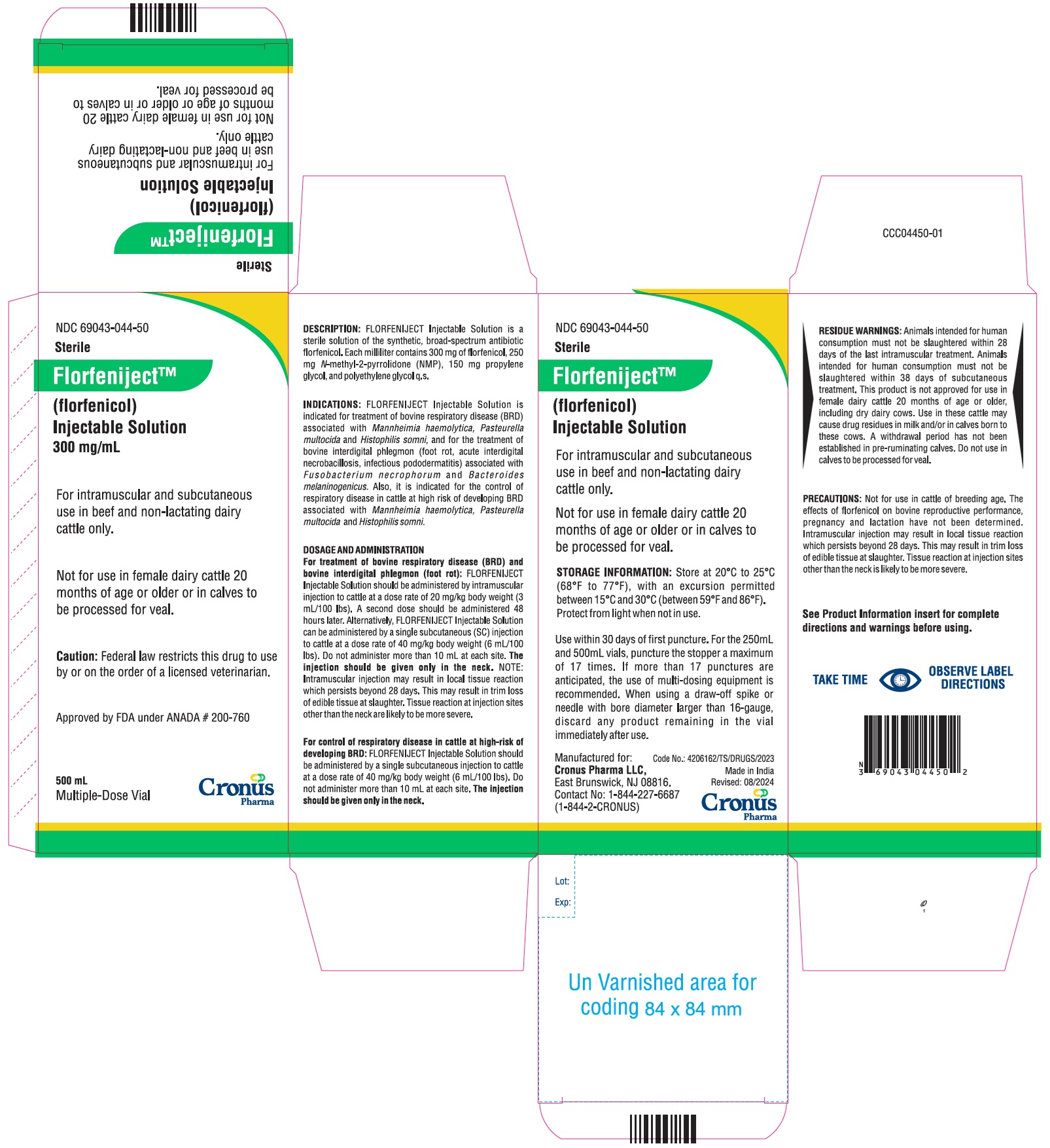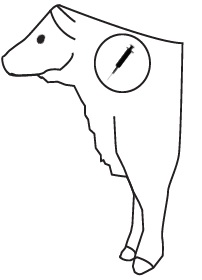 DRUG LABEL: Florfeniject
NDC: 69043-044 | Form: INJECTION, SOLUTION
Manufacturer: Cronus Pharma LLC
Category: animal | Type: PRESCRIPTION ANIMAL DRUG LABEL
Date: 20250103

ACTIVE INGREDIENTS: FLORFENICOL 300 mg/1 mL

Florfeniject™ (florfenicol) Injectable Solution 300 mg/mL

For intramuscular and subcutaneous use in beef and non-lactating dairy cattle only.

Not for use in female dairy cattle 20 months of age or older or in calves to be processed for veal.

CAUTION

Federal law restricts this drug to use by or on the order of a licensed veterinarian.

DESCRIPTION

FLORFENIJECT Injectable Solution is a solution of the synthetic antibiotic florfenicol. Each milliliter of sterile FLORFENIJECT Injectable Solution contains 300 mg of florfenicol, 250 mg N-methyl-2-pyrrolidone (NMP), 150 mg propylene glycol, and polyethylene glycol qs. The chemical name for florfenicol is 2,2-Dichloro-N-[1-(fluoromethyl)-2-hydroxy-2-[4-(methylsulfonyl)phenyl]ethyl] acetamide.

INDICATIONS

FLORFENIJECT Injectable Solution is indicated for treatment of bovine respiratory disease (BRD) associated with Mannheimia haemolytica, Pasteurella multocida, and Histophilus somni, and for the treatment of bovine interdigital phlegmon (foot rot, acute interdigital necrobacillosis, infectious pododermatitis) associated with Fusobacterium necrophorum and Bacteroides melaninogenicus. Also, it is indicated for the control of respiratory disease in cattle at high risk of developing BRD associated with Mannheimia haemolytica, Pasteurella multocida, and Histophilus somni.

DOSAGE AND ADMINISTRATION

For treatment of bovine respiratory disease (BRD) and bovine interdigital phlegmon (foot rot): FLORFENIJECT Injectable Solution should be administered by intramuscular injection to cattle at a dose rate of 20 mg/kg body weight (3 mL/100 lbs). A second dose should be administered 48 hours later. Alternatively, FLORFENIJECT Injectable Solution can be administered by a single subcutaneous (SC) injection to cattle at a dose rate of 40 mg/kg body weight (6 mL/100 lbs). Do not administer more than 10 mL at each site. The injection should be given only in the neck.

NOTE: Intramuscular injection may result in local tissue reaction which persists beyond 28 days. This may result in trim loss of edible tissue at slaughter. Tissue reaction at injection sites other than the neck is likely to be more severe.

For control of respiratory disease in cattle at high-risk of developing BRD: FLORFENIJECT Injectable Solution should be administered by a single subcutaneous injection to cattle at a dose rate of 40 mg/kg body weight (6 mL/100 lbs). Do not administer more than 10 mL at each site. The injection should be given only in the neck.

FLORFENIJECT Injectable Solution DOSAGE GUIDE
ANIMAL WEIGHT (lbs) | IM FLORFENIJECT DOSAGE; 3.0 mL/100 lb Body Weight (mL) | SC FLORFENIJECT DOSAGE 6.0 mL/100 lb Body Weight (mL)
100 | 3.0 | 6.0
200 | 6.0 | 12.0
300 | 9.0 | 18.0
400 | 12.0 | 24.0
500 | 15.0 | 30.0
600 | 18.0 | 36.0
700 | 21.0 | 42.0
800 | 24.0 | 48.0
900 | 27.0 | 54.0
1000 | 30.0 | 60.0

Recommended Injection Location

Do not inject more than 10 mL per injection site.

Clinical improvement should be evident in most treated subjects within 24 hours of initiation of treatment. If a positive response is not noted within 72 hours of initiation of treatment, the diagnosis should be re-evaluated.

CONTRAINDICATIONS

Do not use in animals that have shown hypersensitivity to florfenicol.

USER SAFETY WARNINGS:

NOT FOR HUMAN USE. KEEP OUT OF REACH OF CHILDREN. This product contains materials that can be irritating to skin and eyes. Avoid direct contact with skin, eyes, and clothing. In case of accidental eye exposure, flush with water for 15 minutes. In case of accidental skin exposure, wash with soap and water. Remove contaminated clothing. Consult a physician if irritation persists. Accidental injection of this product may cause local irritation. Consult a physician immediately.

Reproductive and developmental toxicities have been reported in laboratory animals following high, repeated exposures to N-methyl-2- pyrrolidone (NMP). Pregnant women should wear gloves and exercise caution or avoid handling this product.

The Safety Data Sheet (SDS) contains more detailed occupational safety information.

CONTACT INFORMATION:

To report suspected adverse drug events, for technical assistance or to obtain a copy of the SDS, contact Cronus Pharma LLC at 1-844-227-6687. For additional information about adverse drug experience reporting for animal drugs, contact FDA at 1-888-FDA-VETS or http://www.fda.gov/reportanimalae.

PRECAUTIONS:

Not for use in animals intended for breeding purposes. The effects of florfenicol on bovine reproductive performance, pregnancy, and lactation have not been determined. Toxicity studies in dogs, rats, and mice have associated the use of florfenicol with testicular degeneration and atrophy. Intramuscular injection may result in local tissue reaction which persists beyond 28 days. This may result in trim loss of edible tissue at slaughter. Tissue reaction at injection sites other than the neck is likely to be more severe.

RESIDUE WARNINGS:

Animals intended for human consumption must not be slaughtered within 28 days of the last intramuscular treatment. Animals intended for human consumption must not be slaughtered within 38 days of subcutaneous treatment. This product is not approved for use in female dairy cattle 20 months of age or older, including dry dairy cows. Use in these cattle may cause drug residues in milk and/or in calves born to these cows. A withdrawal period has not been established in pre-ruminating calves. Do not use in calves to be processed for veal.

ADVERSE REACTIONS

Inappetence, decreased water consumption, or diarrhea may occur transiently following treatment.

CLINICAL PHARMACOLOGY

The pharmacokinetic disposition of Florfenicol Injectable Solution was evaluated in feeder calves following single intramuscular (IM) administration at the recommended dose of 20 mg/kg body weight. Florfenicol Injectable Solution was also administered intravenously (IV) to the same cattle in order to calculate the volume of distribution, clearance, and percent bioavailability1 (Table 1).

TABLE 1. Pharmacokinetic Parameter Values for Florfenicol Following IM Administration of 20 mg/kg Body Weight to Feeder Calves (n=10).
Parameter | Median | Range
Cmax (µg/mL) | 3.07* | 1.43 - 5.60
tmax (hr) | 3.33 | 0.75 - 8.00
T ½ (hr) | 18.3† | 8.30 - 44.0
AUC (µg.min/mL) | 4242 | 3200 - 6250
Bioavailability (%) | 78.5 | 59.3 - 106
Vdss (L/kg)‡ | 0.77 | 0.68 - 0.85
Clt (mL/min/kg)‡ | 3.75 | 3.17 - 4.31

Cmax Maximum serum concentration

Tmax Time at which Cmax is observed

T ½ Biological half-life

AUC Area under the curve

Vdss Volume of distribution at steady state

Clt Total body clearance

*harmonic mean

†mean value

‡following IV administration

Florfenicol was detectable in the serum of most animals through 60 hours after intramuscular administration with a mean concentration of 0.19 µg/mL. The protein binding of florfenicol was 12.7%, 13.2%, and 18.3% at serum concentrations of 0.5, 3.0, and 16.0 µg/mL, respectively.

MICROBIOLOGY

Florfenicol is a synthetic, broad-spectrum antibiotic active against many Gram negative and Gram-positive bacteria isolated from domestic animals. It acts by binding to the 50S ribosomal subunit and inhibiting bacterial protein synthesis. Florfenicol is generally considered a bacteriostatic drug, but exhibits bactericidal activity against certain bacterial species. In vitro studies demonstrate that florfenicol is active against the bovine respiratory disease (BRD) pathogens Mannheimia haemolytica, Pasteurella multocida, and Histophilus somni, and that florfenicol exhibits bactericidal activity against strains of M. haemolytica and H. somni. Clinical studies confirm the efficacy of florfenicol against BRD as well as against commonly isolated bacterial pathogens in bovine interdigital phlegmon including Fusobacterium necrophorum and Bacteroides melaninogenicus.

The minimum inhibitory concentrations (MICs) of florfenicol for BRD organisms were determined using isolates obtained from natural infections from 1990 to 1993. The MICs for interdigital phlegmon organisms were determined using isolates obtained from natural infections from 1973 to 1997 (Table 2).

TABLE 2. Florfenicol Minimum Inhibitory Concentration (MIC) Values* of Indicated Pathogens Isolated From Natural Infections of Cattle.
Indicated pathogens | Year of isolation | Isolate Numbers | MIC 50†; (µg/mL) | MIC 90†; (µg/mL)
Mannheimia haemolytica | 1990 to 1993 | 398 | 0.5 | 1
Pasteurella multocida | 1990 to 1993 | 350 | 0.5 | 0.5
Histophilis somni | 1990 to 1993 | 66 | 0.25 | 0.5
Fusobacterium necrophorum | 1973 to 1997 | 33 | 0.25 | 0.25
Bacteroides melaninogenicus | 1973 to 1997 | 20 | 0.25 | 0.25

*The correlation between the in vitro susceptibility data and clinical effectiveness is unknown.

†The lowest MIC to encompass 50% and 90% of the most susceptible isolates, respectively.

ANIMAL SAFETY

A 10x safety study was conducted in feeder calves. Two intramuscular injections of 200 mg/kg were administered at a 48-hour interval. The calves were monitored for 14 days after the second dose. Marked anorexia, decreased water consumption, decreased body weight, and increased serum enzymes were observed following dose administration. These effects resolved by the end of the study.

A 1x, 3x, and 5x (20, 60, and 100 mg/kg) safety study was conducted in feeder calves for 3x the duration of treatment (6 injections at 48-hour intervals). Slight decrease in feed and water consumption was observed in the 1x dose group. Decreased feed and water consumption, body weight, urine pH, and increased serum enzymes, were observed in the 3x and 5x dose groups. Depression, soft stool consistency, and dehydration were also observed in some animals (most frequently at the 3x and 5x dose levels), primarily near the end of dosing.

A 43-day controlled study was conducted in healthy cattle to evaluate effects of florfenicol injectable solution administered at the recommended dose on feed consumption. Although a transient decrease in feed consumption was observed, Florfenicol Injectable Solution administration had no long-term effect on body weight, rate of gain, or feed consumption.

STORAGE INFORMATION

Store at 20°C to 25°C (68°F to 77°F), with an excursion permitted between 15°C and 30°C (between 59°F and 86°F).
Protect from light when not in use.

Use within 30 days of first puncture. For the 100mL vials, puncture the stopper a maximum of 3 times. For the 250mL and 500mL vials, puncture the stopper a maximum of 17 times. If more than the specified punctures are anticipated, the use of multi-dosing equipment is recommended. When using a draw-off spike or needle with bore diameter larger than 16-gauge, discard any product remaining in the vial immediately after use.

HOW SUPPLIED

FLORFENIJECT Injectable Solution is packaged in 100 mL (NDC 69043-044-10), 250 mL (NDC 69043-044-25), and 500 mL (NDC 69043-044-50) glass sterile multiple-dose vials.

REFERENCE

1. Lobell RD, Varma KJ, et al. Pharmacokinetics of florfenicol following intravenous and intramuscular doses to cattle. J Vet Pharmacol Therap. 1994;17:253-258.

Florfeniject™ is the trademark of Cronus Pharma LLC

Approved by FDA under ANADA # 200-760

Manufactured for:
Cronus Pharma LLC,
East Brunswick, NJ 08816.
Contact No: 1-844-227-6687
(1-844-2-CRONUS)
Made in India

PC044-00

Code No.: 4206162/TS/DRUGS/2023

January 2024

PACKAGE LABEL.PRINCIPAL DISPLAY PANEL

NDC 69043-044-10

Sterile

Florfeniject™

(florfenicol)

Injectable Solution

300 mg/mL

For intramuscular and subcutaneous use in beef and non-lactating dairy cattle only.

Not for use in female dairy cattle 20 months of age or older or in calves to be processed for veal.

Caution: Federal law restricts this drug to use by or on the order of a licensed veterinarian.

Approved by FDA under ANADA # 200-760

100 mL

Multiple-Dose Vial

PACKAGE LABEL.PRINCIPAL DISPLAY PANEL

NDC 69043-044-25

Sterile

Florfeniject™

(florfenicol)

Injectable Solution

300 mg/mL

For intramuscular and subcutaneous use in beef and non-lactating dairy cattle only.

Not for use in female dairy cattle 20 months of age or older or in calves to be processed for veal.

Caution: Federal law restricts this drug to use by or on the order of a licensed veterinarian.

Approved by FDA under ANADA # 200-760

250 mL

Multiple-Dose Vial

PACKAGE LABEL

NDC 69043-044-50

Sterile

Florfeniject™

(florfenicol)

Injectable Solution

300 mg/mL

For intramuscular and subcutaneous use in beef and non-lactating dairy cattle only.

Not for use in female dairy cattle 20 months of age or older or in calves to be processed for veal.

Caution: Federal law restricts this drug to use by or on the order of a licensed veterinarian.

Approved by FDA under ANADA # 200-760

500 mL

Multiple-Dose Vial